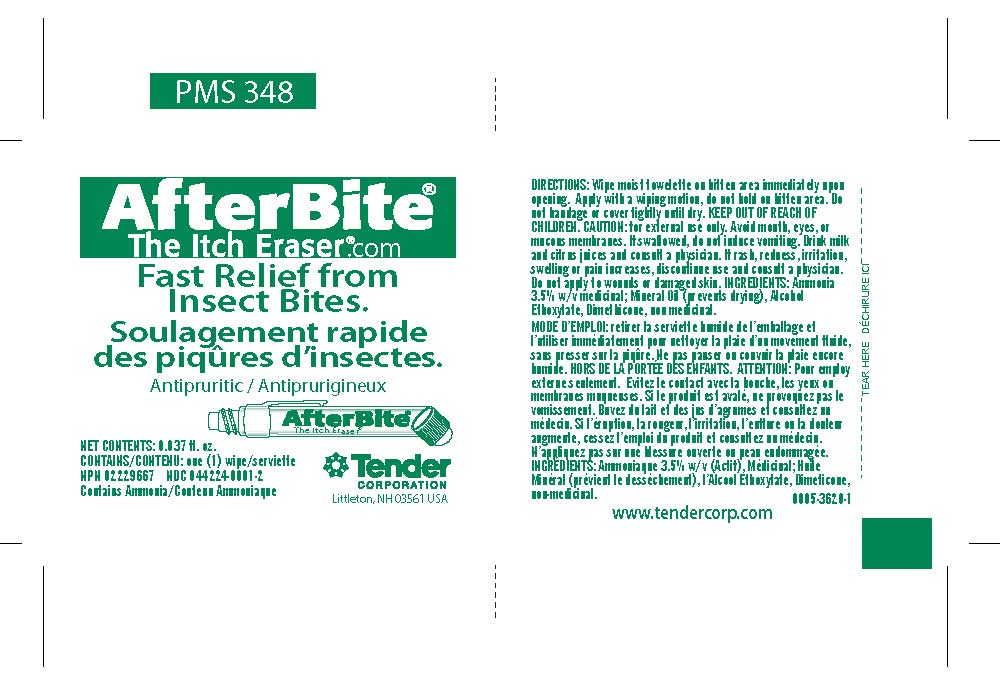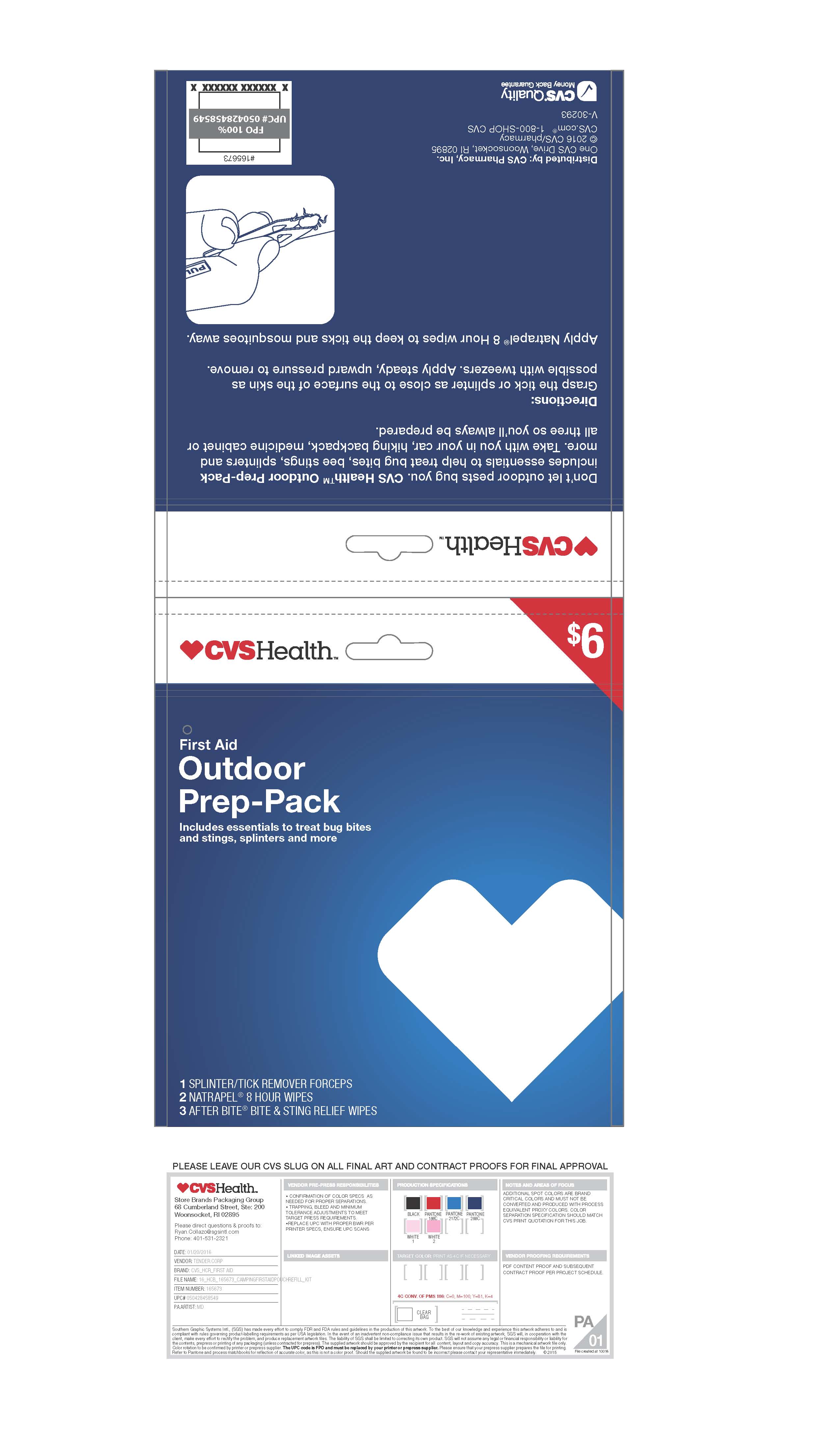 DRUG LABEL: CVS Health First Aid Outdoor Prep-Pack
NDC: 69842-407 | Form: KIT | Route: TOPICAL
Manufacturer: CVS
Category: otc | Type: HUMAN OTC DRUG LABEL
Date: 20170120

ACTIVE INGREDIENTS: AMMONIA 30 mg/1 mL
INACTIVE INGREDIENTS: LIGHT MINERAL OIL; C12-13 ALCOHOLS; DIMETHICONE 1000; WATER

CVS Health First Aid Outdoor Prep-Pack

Active Ingredient

Ammonia 3.5%

Purpose

Counterirritant

Use

Temporarily protects and helps relieve minor skin irriatation and itching due to

- insect bites and stings
- poison ivy, oak or sumac

Warnings

Warning: For external use only.

Keep out of reach of children: If swallowed, get medical help or contact a Poison Control Center right away.

Stop use and ask a doctor if

- condition worsens
- symptoms last more than 7 days or clear up and occur again within a few days

When using this product

Do not get into eyes

Directions

Adults and children under 2 years and older dab directly on bite or sting, rub gently and re-apply as needed

Children under 2 years ask a doctor

Inactive Ingredients

Alcohol Ethoxylate, Dimethicone, Mineral Oil and Purified Water

PACKAGE LABEL

After Bite

The Itch Eraser

Fast Relief from Insect Bites.

Net Contents: 0.037fl. oz.

Contains: One (1) Wipe

Contains Ammonia

Tender Corporation

Littleton, NH 03561